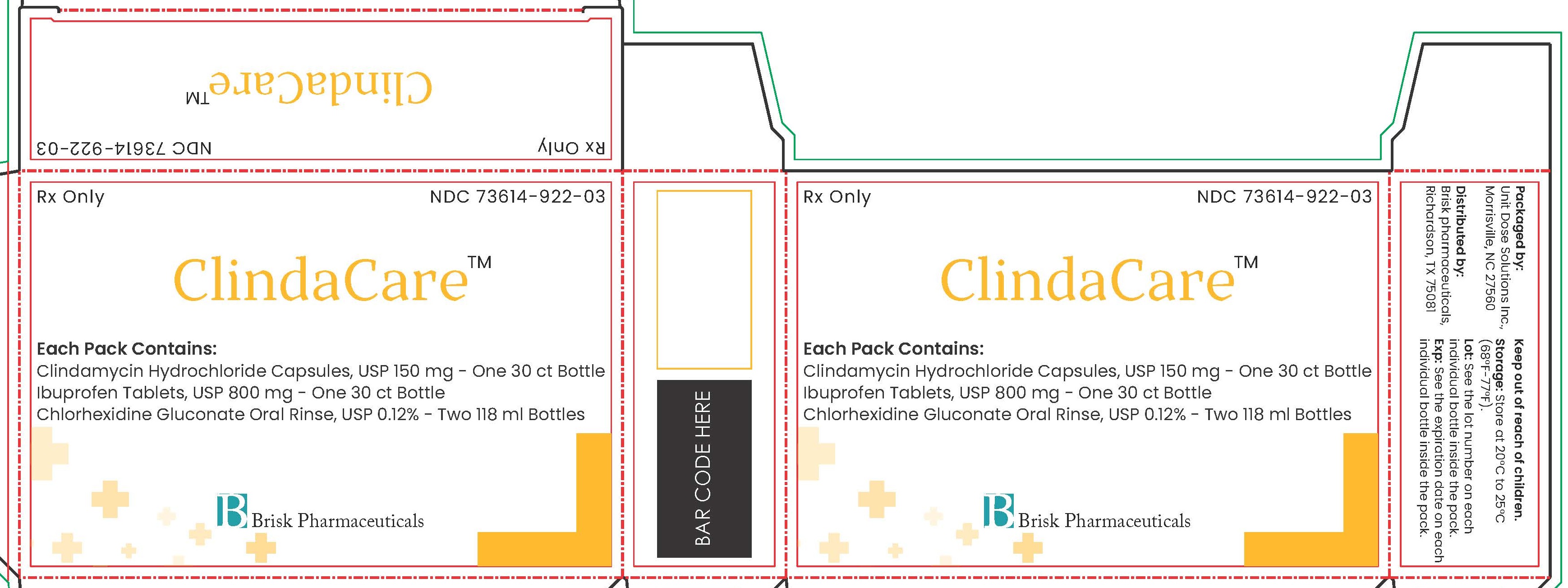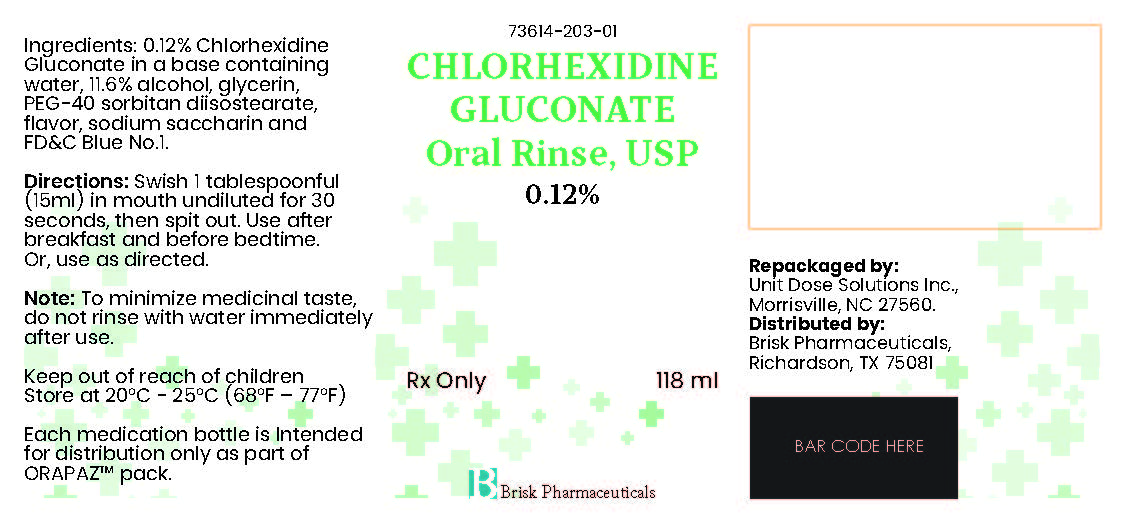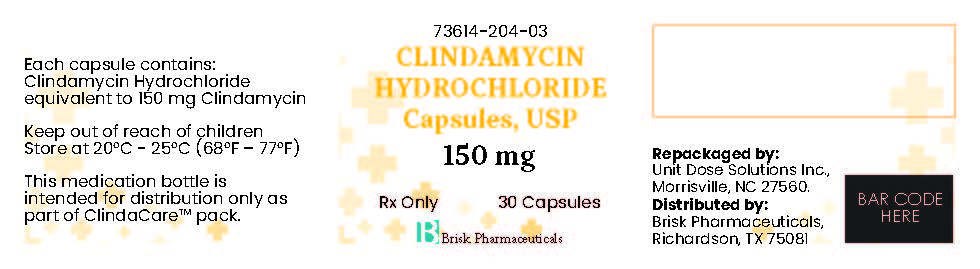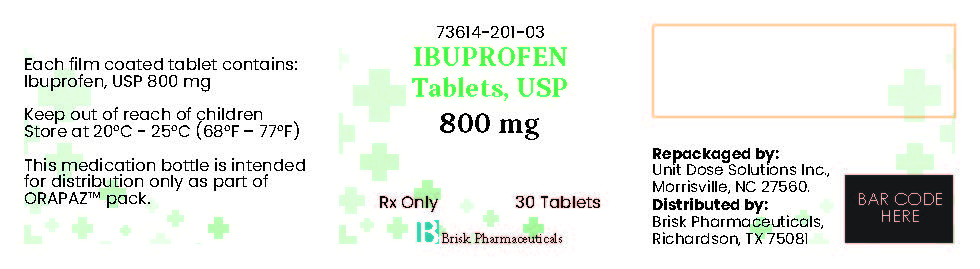 DRUG LABEL: ClindaCare
NDC: 73614-922 | Form: KIT | Route: ORAL
Manufacturer: Brisk Pharmaceuticals
Category: prescription | Type: HUMAN PRESCRIPTION DRUG LABEL
Date: 20250210

ACTIVE INGREDIENTS: IBUPROFEN 800 mg/1 1; CHLORHEXIDINE GLUCONATE 1.2 mg/1 mL; CHLORHEXIDINE GLUCONATE 1.2 mg/1 mL; CLINDAMYCIN HYDROCHLORIDE 150 mg/1 1
INACTIVE INGREDIENTS: CROSCARMELLOSE SODIUM; MAGNESIUM STEARATE; STEARIC ACID; POLYETHYLENE GLYCOL, UNSPECIFIED; SODIUM STARCH GLYCOLATE TYPE A POTATO; TALC; STARCH, CORN; SILICON DIOXIDE; MICROCRYSTALLINE CELLULOSE; TITANIUM DIOXIDE; ALCOHOL; GLYCERIN; WATER; FD&C BLUE NO. 1; SACCHARIN SODIUM; PEG-40 SORBITAN DIISOSTEARATE; ALCOHOL; GLYCERIN; WATER; FD&C BLUE NO. 1; SACCHARIN SODIUM; PEG-40 SORBITAN DIISOSTEARATE; SILICON DIOXIDE; STARCH, CORN; LACTOSE MONOHYDRATE; POTASSIUM HYDROXIDE; MAGNESIUM STEARATE; PROPYLENE GLYCOL; SHELLAC; TALC; GELATIN, UNSPECIFIED; FD&C BLUE NO. 1; FERRIC OXIDE YELLOW; TITANIUM DIOXIDE; FERROSOFERRIC OXIDE

ClindaCare

DESCRIPTION

Rx Only

NDC 73614-922-03

ClindaCare™

Each Pack Contains:

Clindamycin Hydrochloride Capsules, USP 150 mg - One 30 ct Bottle

Ibuprofen Tablets, USP 800 mg - One 30 ct Bottle

Chlorhexidine Gluconate Oral Rinse, USP 0.12% - Two 118 ml Bottles

Brisk Pharmaceuticals

DESCRIPTION

Packaged by:

Unit Dose Solutions Inc.,

Morrisville, NC 27560

Distributed by:

Brisk pharmaceuticals,

Richardson, TX 75081

Keep out of reach of children.

Storage: Store at 20°C to 25°C

(68°F-77°F).

Lot: See the lot number on each

individual bottle inside the pack.

Exp: See the expiration date on each

individual bottle inside the pack.